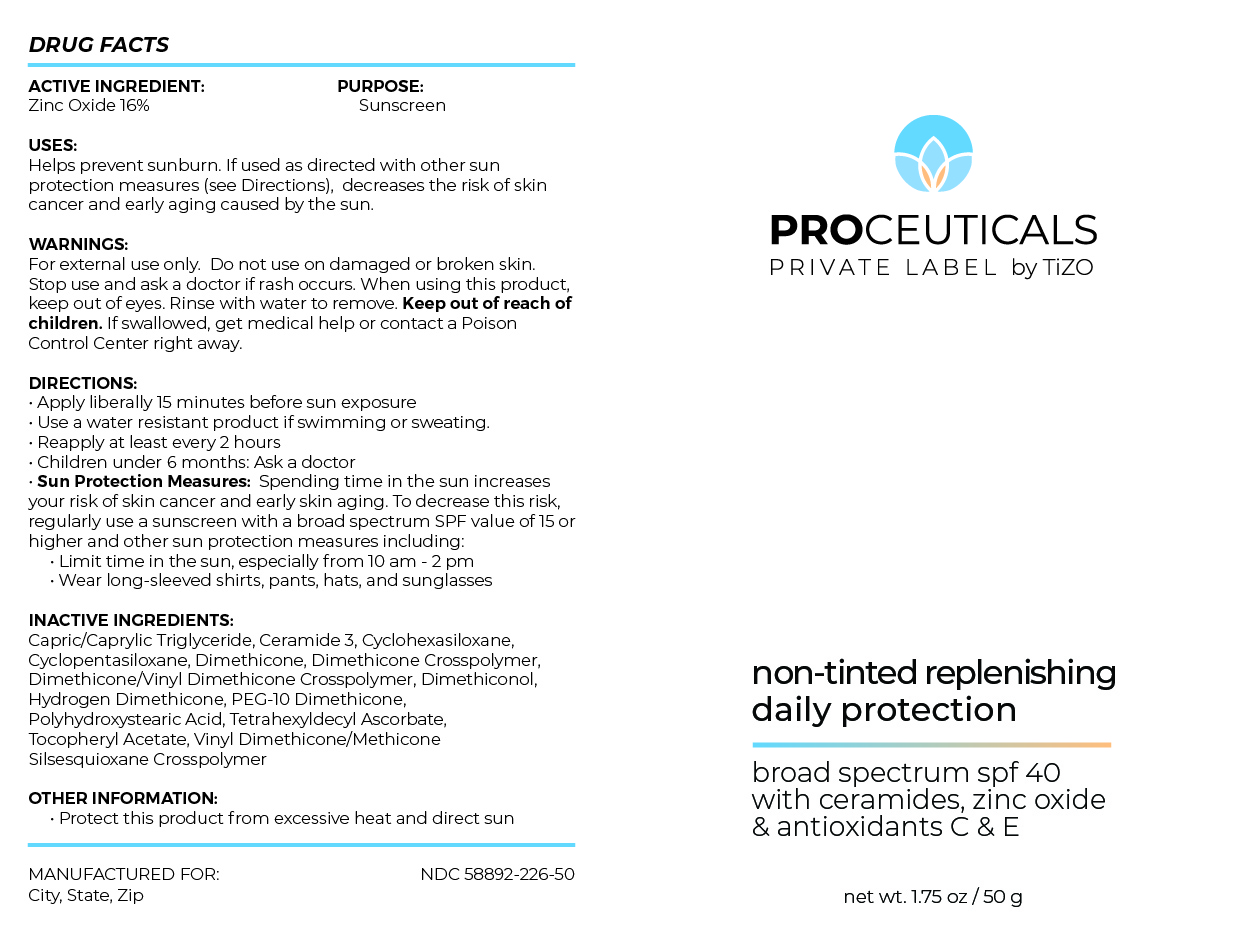 DRUG LABEL: Proceuticals Private Label by TiZO non-tinted replenishing daily protection
NDC: 58892-226 | Form: CREAM
Manufacturer: Fallien Cosmeceuticals, Ltd
Category: otc | Type: HUMAN OTC DRUG LABEL
Date: 20240913

ACTIVE INGREDIENTS: ZINC OXIDE 160 mg/1 g
INACTIVE INGREDIENTS: PEG-10 DIMETHICONE (600 CST); MEDIUM-CHAIN TRIGLYCERIDES; CYCLOMETHICONE 6; VINYL DIMETHICONE/METHICONE SILSESQUIOXANE CROSSPOLYMER; POLYHYDROXYSTEARIC ACID (2300 MW); CYCLOMETHICONE 5; TETRAHEXYLDECYL ASCORBATE; .ALPHA.-TOCOPHEROL ACETATE; DIMETHICONE CROSSPOLYMER (450000 MPA.S AT 12% IN CYCLOPENTASILOXANE); HYDROGEN DIMETHICONE (20 CST); CERAMIDE NP; DIMETHICONE/VINYL DIMETHICONE CROSSPOLYMER (SOFT PARTICLE); DIMETHICONE 20; DIMETHICONOL (2000 CST)

ACTIVE INGREDIENTS:

Zinc Oxide 16%

PURPOSE:Sunscreen

USES: Helps prevent sunburn. If used as directed
with other sun protection measures (see
Directions), decreases the risk of skin cancer
and early skin aging caused by the sun.

DIRECTIONS:
• Apply liberally 15 minutes before sun exposure
• Use a water resistant product if swimming or sweating.
• Reapply at least every 2 hours
• Children under 6 months: Ask a doctor
• Sun Protection Measures: Spending time in the sun increases
your risk of skin cancer and early skin aging. To decrease this risk,
regularly use a sunscreen with a broad spectrum SPF value of 15 or
higher and other sun protection measures including:
• Limit time in the sun, especially from 10 am - 2 pm
• Wear long-sleeved shirts, pants, hats, and sunglasses

INACTIVE INGREDIENTS:
Capric/Caprylic Triglyceride, Ceramide 3, Cyclohexasiloxane,
Cyclopentasiloxane, Dimethicone, Dimethicone Crosspolymer,
Dimethicone/Vinyl Dimethicone Crosspolymer, Dimethiconol,
Hydrogen Dimethicone, PEG-10 Dimethicone,
Polyhydroxystearic Acid, Tetrahexyldecyl Ascorbate,
Tocopheryl Acetate, Vinyl Dimethicone/Methicone
Silsesquioxane Crosspolymer

OTHER INFORMATION: • Protect this product
from excessive heat and direct sun • May stain
some fabrics

WARNINGS:
For external use only. Do not use on damaged or broken skin.
Stop use and ask a doctor if rash occurs. When using this product,
keep out of eyes. Rinse with water to remove. Keep out of reach of
children. If swallowed, get medical help or contact a Poison
Control Center right away.

Keep out of the reach of children.

DOSAGE AND ADMINISTRATION

Helps prevent sunburn. If used as directed
with other sun protection measures (see
Directions), decreases the risk of skin cancer
and early skin aging caused by the sun.

Apply liberally 15 minutes befor sun exposure.

Principal Display Panel – 50g Bottle Label

PROCEUTICALS

PRIVATE LABEL by TiZO

non-tinted replenishing
daily protection

broad spectrum spf 40
with ceramides, zinc oxide
& antioxidants C & E

net wt. 1.75 oz / 50 g

Graphic-Untitled